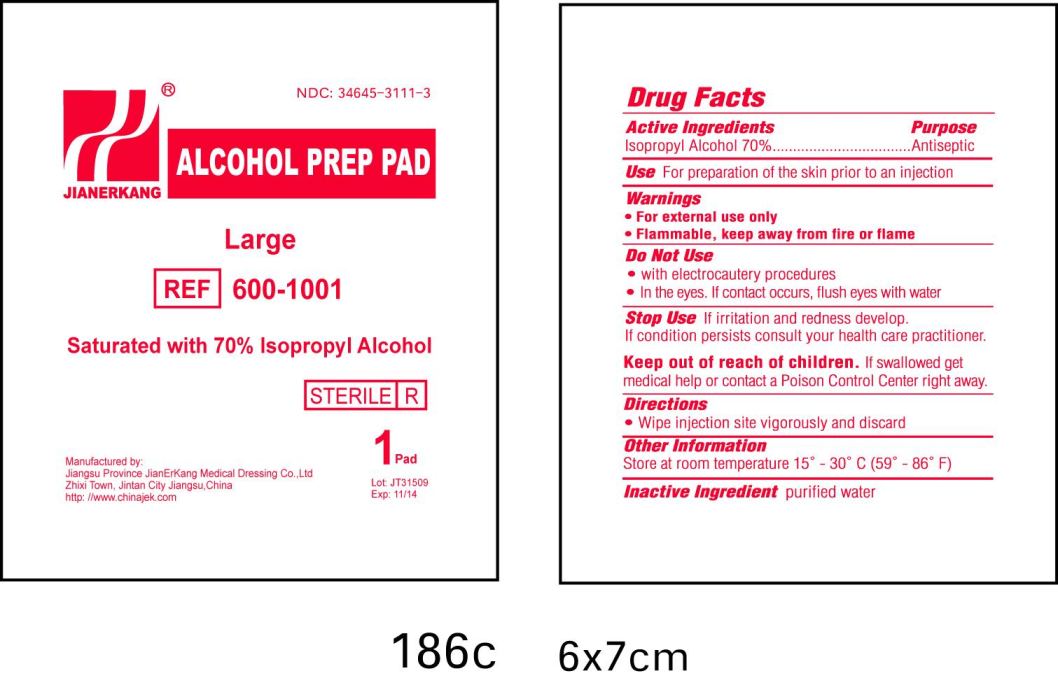 DRUG LABEL: Alcohol Prep Pad
NDC: 34645-3111 | Form: SWAB
Manufacturer: Jianerkang Medical Co., Ltd
Category: otc | Type: HUMAN OTC DRUG LABEL
Date: 20231023

ACTIVE INGREDIENTS: ISOPROPYL ALCOHOL 70 mL/100 mL
INACTIVE INGREDIENTS: WATER

Drug Facts

Active Ingredients

Isopropyl Alcohol 70%

Purpose

Antiseptic

Use

For preparation of the skin prior to an injection

Warnings

For external use only

Flammable, keep away from fire or flame

Do Not Use

with electrocautery procedures

in the eyes, if contact occurs, flush eyes with water

Stop Use

If irritation and redness develop.

If condition persists consult your health care practitioner

Keep out of reach of children

If swallowed, get medical help or contact Poison Control Center right away

Directions

Wipe injection site vigorously and discard

Other Information

Store at room temperature 15 -30 C (59 -86 F)oooo

Inactive Ingredient

purified water